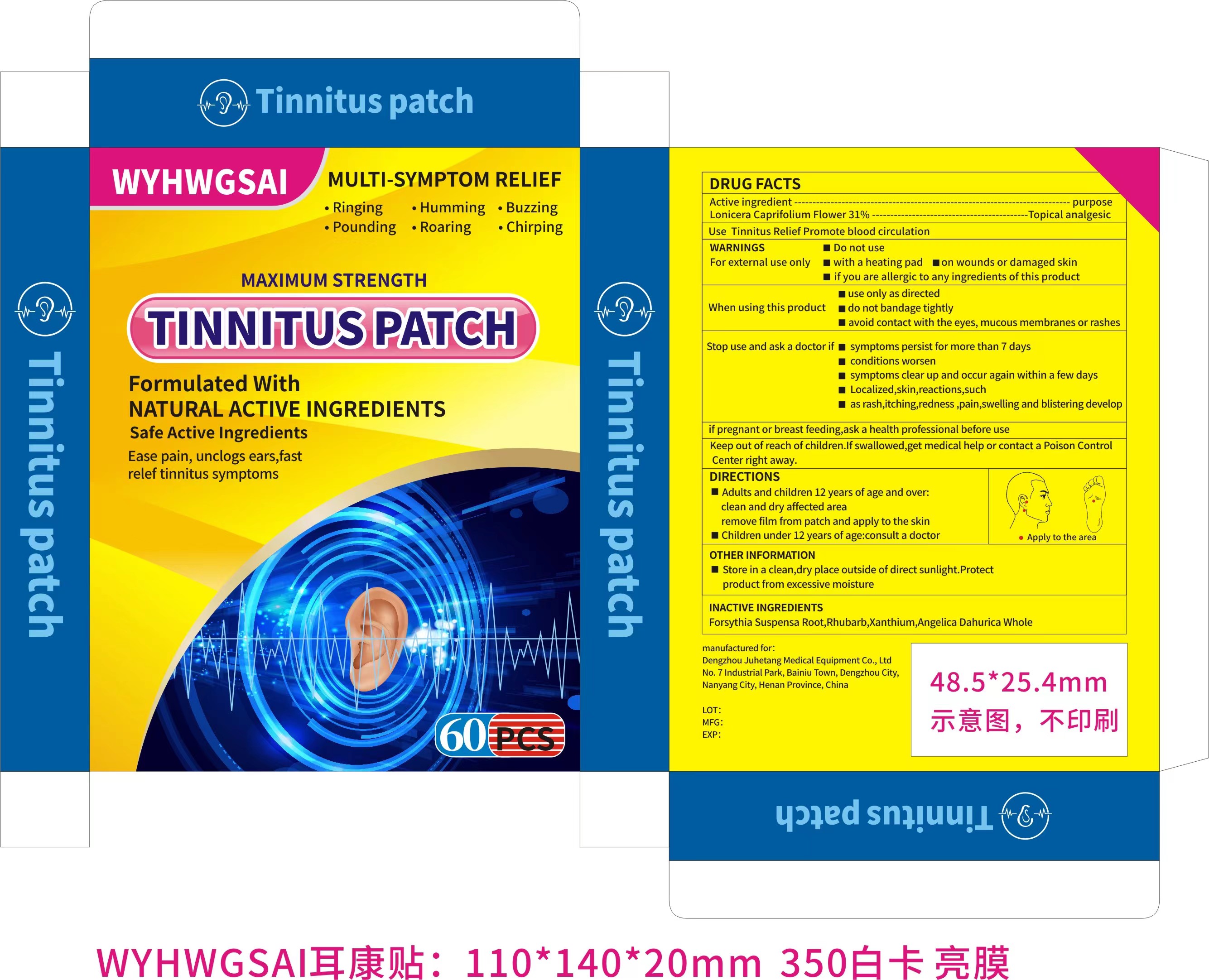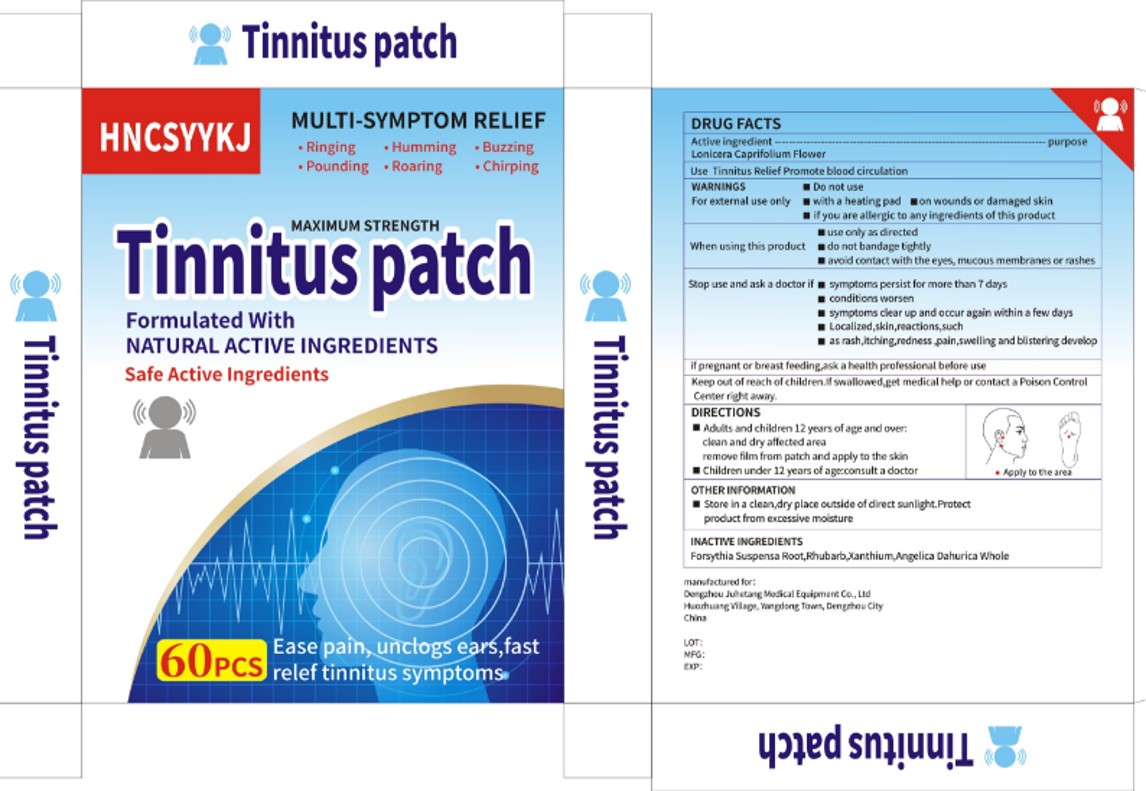 DRUG LABEL: Tinnitus patch
NDC: 84171-201 | Form: PATCH
Manufacturer: Dengzhou Juhetang Medical Equipment Co., Ltd
Category: otc | Type: HUMAN OTC DRUG LABEL
Date: 20240307

ACTIVE INGREDIENTS: LONICERA CAPRIFOLIUM FLOWER 31 g/100 1
INACTIVE INGREDIENTS: XANTHIUM SIBIRICUM ROOT; RHUBARB; FORSYTHIA SUSPENSA ROOT; ANGELICA DAHURICA WHOLE

Tinnitus patch

Tinnitus patch

ACTIVE INGREDIENT

Lonicera Caprifolium Flower 31%

PURPOSE

Topical analgesic

INDICATIONS AND USAGE

Tinnitus Relief Promote blood circulation

WARNINGS

For external use only

DO NOT USE

with a heating pad
on wounds or damaged skin
if you are allergic to any ingredients of this product

WHEN USING

use only as directed
do not bandage tightly
avoid contact with the eyes, mucous membranes or rashes

STOP USE

symptoms persist for more than 7 days
conditions worsen
symptoms clear up and occur again within a few days
Localized,skin,reactions,such
as rash,itching,redness ,pain,swelling and blistering develop

Keep out of reach of children.lf swallowed,get medical help or contact a Poison Control Center right away.

DOSAGE AND ADMINISTRATION

Adults and children 12 years of age and over:

clean and dry affected area

remove film from patch and apply to the skin

Children under 12 years of age:consult a doctor

STORAGE AND HANDLING

Store in a clean,dry place outside of direct sunlight.Protect product from excessive moisture

INACTIVE INGREDIENT

forsythia suspensa root
Rhubarb
Xanthium
Angelica Dahurica Whole